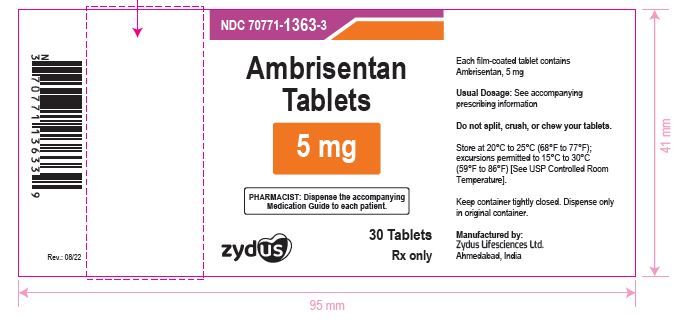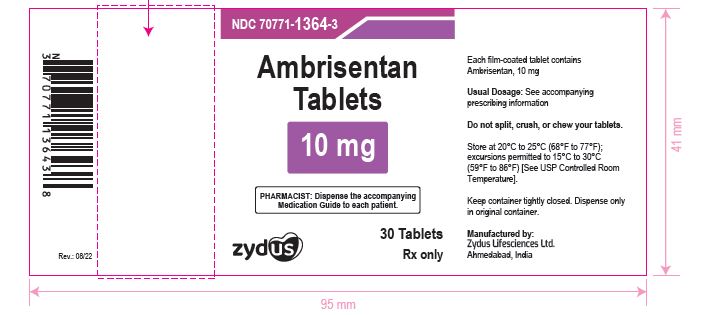 DRUG LABEL: Ambrisentan
NDC: 70771-1363 | Form: TABLET, FILM COATED
Manufacturer: Zydus Lifesciences Limited
Category: prescription | Type: HUMAN PRESCRIPTION DRUG LABEL
Date: 20241125

ACTIVE INGREDIENTS: AMBRISENTAN 5 mg/1 1
INACTIVE INGREDIENTS: CROSCARMELLOSE SODIUM; LACTOSE MONOHYDRATE; LECITHIN, SOYBEAN; MAGNESIUM STEARATE; CELLULOSE, MICROCRYSTALLINE; POLYETHYLENE GLYCOL, UNSPECIFIED; POVIDONE; TALC; TITANIUM DIOXIDE; FD&C RED NO. 40; ALUMINUM OXIDE; POLYVINYL ALCOHOL, UNSPECIFIED

AMBRISENTAN Tablets

PACKAGE LABEL.PRINCIPAL DISPLAY PANEL

NDC 70771-1363-3

Ambrisentan Tablets, 5 mg

30 Tablets

Rx only

NDC 70771-1364-3

Ambrisentan Tablets, 10 mg

30 Tablets

Rx only